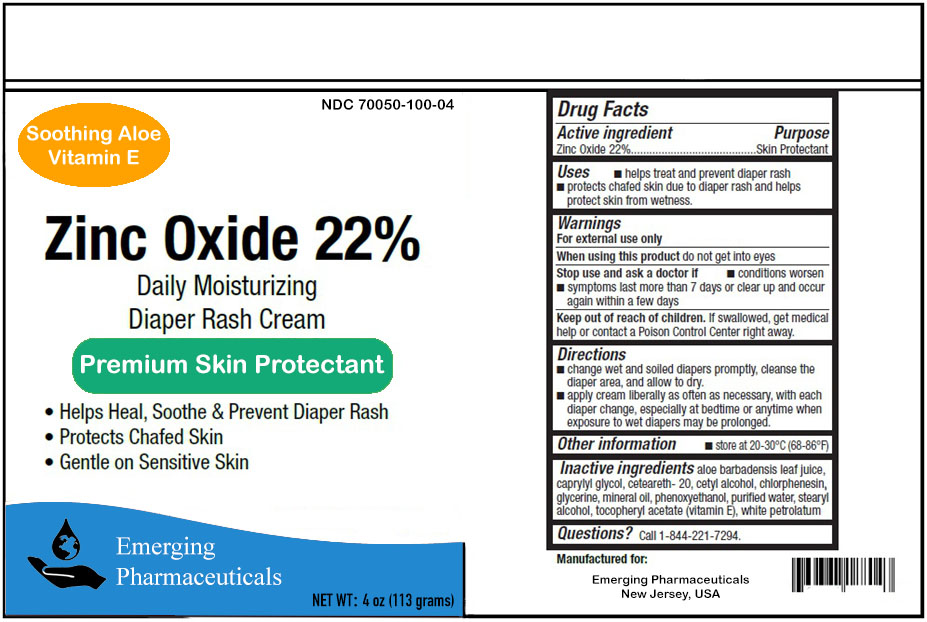 DRUG LABEL: Zinc Oxide Cream
NDC: 70050-100 | Form: CREAM
Manufacturer: Emerging Pharma, LLC
Category: otc | Type: HUMAN OTC DRUG LABEL
Date: 20220501

ACTIVE INGREDIENTS: ZINC OXIDE 22 g/100 g
INACTIVE INGREDIENTS: ALOE VERA LEAF; CAPRYLYL GLYCOL; POLYOXYL 20 CETOSTEARYL ETHER; CETYL ALCOHOL; CHLORPHENESIN; GLYCERIN; MINERAL OIL; PHENOXYETHANOL; WATER; STEARYL ALCOHOL; .ALPHA.-TOCOPHEROL ACETATE; WHITE PETROLATUM

Zinc Oxide Cream

Active ingredient

Zinc Oxide 22%

Purpose

Skin Protectant

Uses

• helps treat and prevent diaper rash
• protects chafed skin due to diaper rash and helps protect skin from wetness.

Warnings

For external use only

When using this product do not get into eyes

Stop use and ask a doctor if

• conditions worsen
• symptoms last more than 7 days or clear up and occur again within a few days

Keep out of reach of children. If swallowed, get medical help or contact a Poison Control Center right away.

Directions

- Change wet and soiled diapers promptly, cleanse the diaper area, and allow to dry.
- Apply cream liberally as often as necessary, with each diaper change, especially at bedtime or anytime when exposure to wet diapers may be prolonged.

Other information

• store at 20-30°C (68-86°F)

Inactive ingredients

aloe barbadensis leaf juice, caprylyl glycol, ceteareth- 20, cetyl alcohol, chlorphenesin, glycerine, mineral oil, phenoxyethanol, purified water, stearyl alcohol, tocopheryl acetate (vitamin E), white petrolatum

Questions ?

Call 1-844-221-7294.

Manufactured for

Emerging Pharmaceuticals
New Jersey, USA

Package Label

NDC 70050-100-04 NET WT: 4 oz (113 grams)